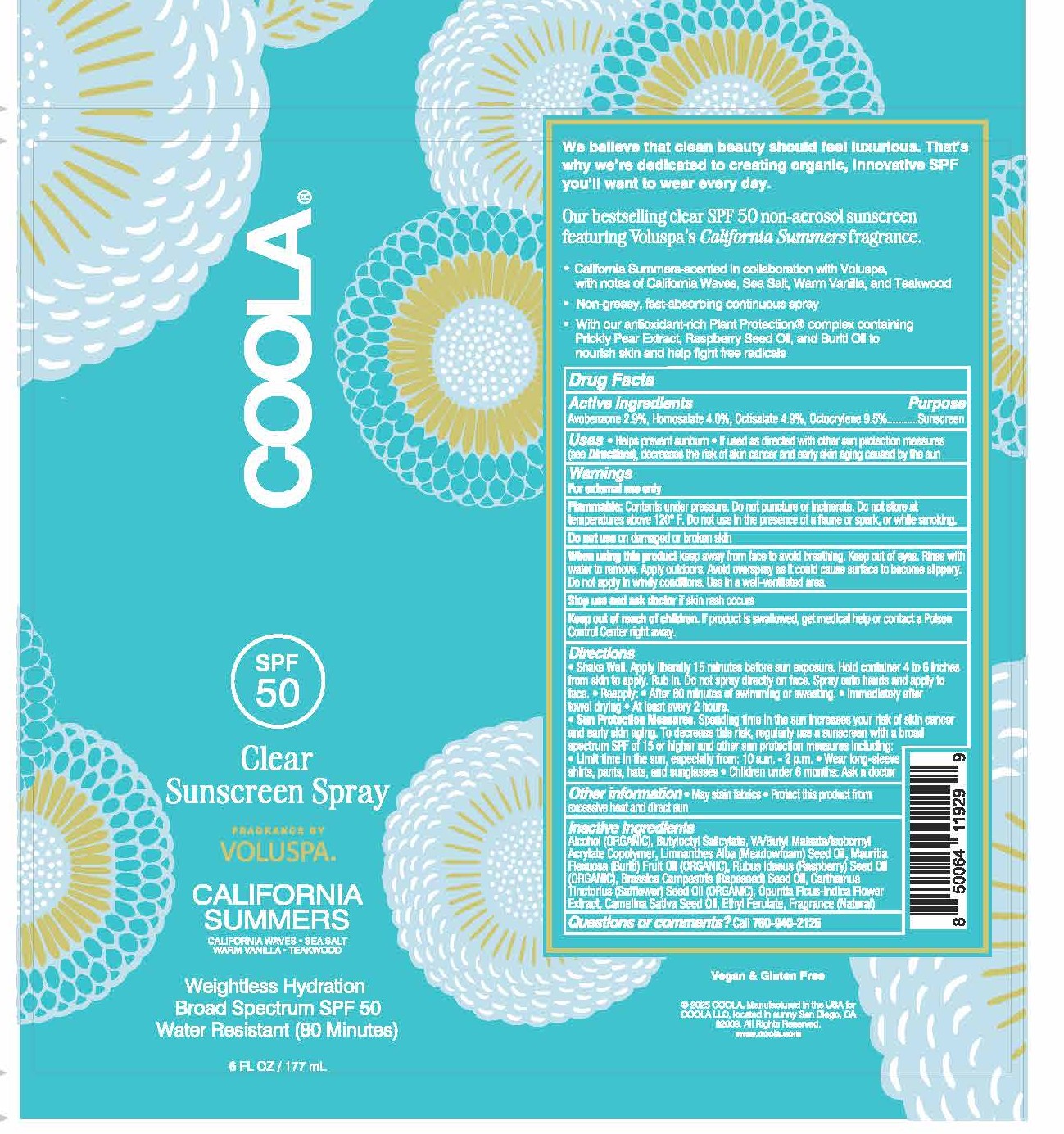 DRUG LABEL: Coola Clear California Summers
NDC: 79753-104 | Form: SPRAY
Manufacturer: COOLA, LLC
Category: otc | Type: HUMAN OTC DRUG LABEL
Date: 20250519

ACTIVE INGREDIENTS: OCTOCRYLENE 10 g/100 g; HOMOSALATE 4.08 g/100 g; AVOBENZONE 3 g/100 g; OCTISALATE 5 g/100 g
INACTIVE INGREDIENTS: ALCOHOL 71.25 g/100 g; OPUNTIA FICUS-INDICA FLOWER 0.002 g/100 g; MONOISOBUTYL MALEATE 1 g/100 g; BUTYLOCTYL SALICYLATE 4.8 g/100 g; RUBUS IDAEUS (RASPBERRY) SEED OIL 0.01 g/100 g; CAMELINA SATIVA SEED OIL 0.002 g/100 g; CARTHAMUS TINCTORIUS (SAFFLOWER) SEED OIL 0.01 g/100 g; ETHYL FERULATE 0.7 g/100 g; LIMNANTHES ALBA (MEADOWFOAM) SEED OIL 0.01 g/100 g; BRASSICA CAMPESTRIS (RAPESEED) SEED OIL 0.006 g/100 g; MAURITIA FLEXUOSA FRUIT OIL 0.01 g/100 g

COOLA Clear Sunscreen Spray SPF 50 6 FL OZ - California Summers (01-DBM-105)

Active Ingredients

Avobenzone 2.9%, Homosalate 4.0%, Octisalate 4.9%, Octocrylene 9.5%

Purpose

Sunscreeen

INDICATIONS AND USAGE

Uses -Helps prevent sunburn -If used as directed with other sun protection measures (see Directions), decreases the risk of skin cancer and early skin aging caused by the sun

Warnings

For external use only

Flammable: Contents under pressure. Do not puncture or incinerate. Do not store at temperatures about 120ºF. Do not use in the presence of a flame or spark, or while smoking.

Keep out of reach of children. If product is swallowed, get medical help or contact a Poison Control Center right away.

When using this product keep away from face to avoid breaking. Keep out of eyes. Rinse with water to remove. Apply outdoors. Avoid overspray as it could cause surface to become slippery. Do not apply in windy conditions. Use in a well-venitilated area.

Stop use and ask doctor if skin rash occurs.

Do not use on damaged or broken skin.

DOSAGE AND ADMINISTRATION

Shake Well. Apply liberally 15 minutes before sun exposure. Hold container 4 to 6 inches from skin to apply. Rub in. Do not spray directly on face. Spray onto hands and apply to face. -Reapply: -After 80 minutes of swimming or sweating. -Immediately after towel drying. -At least every 2 hours.

-Sun protection measures. Spending time in the sun increases your risk of skin cancer and early skin aging. To decrease this risk, regularly use a sunscreen with a broad specturm SPF of 15 or higher and other sun protection measures including: -Limit time in the sun, especially from: 10am - 2pm. -Wear long sleeve shirt, pants, hat and sunglasses -Children under 6 months; Ask a doctor

Questions or comments? Call 760-940-2125

INACTIVE INGREDIENT

Alcohol (ORGANIC), Butyloctyl Salicylate, VA/Butyl Maleate/Isobornyl Acrylate Copolymer, Limnanthes Alba (Meadowfoam) Seed Oil, Mauritia Flexuose (Buriti) Fruit Oil (ORGANIC), Rubus Idaeus (Raspberry) Seed Oil (ORGANIC), Brassica Campestris (Rapeseed) Seed Oil, Carthamus Tinctorius (Safflower) Seed Oil (ORGANIC), Opuntia Ficus-Indica Flower Extract, Camelina Sativa Seed Oil, Ethyl Ferulate, Fragrance (Natural)

Other Information -May stain fabrics -Protect this product from excessive heat and direct sun